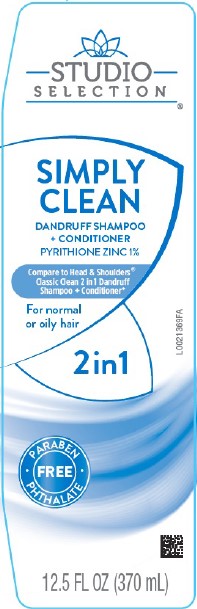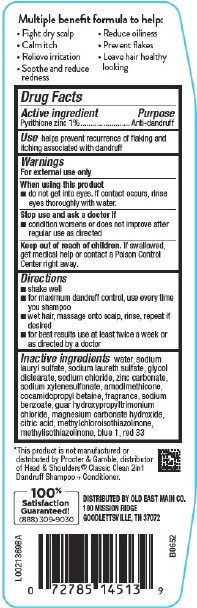 DRUG LABEL: 2 in 1 Dandruff
NDC: 55910-311 | Form: SHAMPOO
Manufacturer: Old East Main Co.
Category: otc | Type: HUMAN OTC DRUG LABEL
Date: 20260302

ACTIVE INGREDIENTS: PYRITHIONE ZINC 10 mg/1 mL
INACTIVE INGREDIENTS: SODIUM LAURYL SULFATE; SODIUM LAURETH SULFATE; GLYCOL DISTEARATE; SODIUM CHLORIDE; ZINC CARBONATE; SODIUM XYLENESULFONATE; AMODIMETHICONE (800 CST); COCAMIDOPROPYL BETAINE; SODIUM BENZOATE; GUAR HYDROXYPROPYLTRIMONIUM CHLORIDE (1.7 SUBSTITUENTS PER SACCHARIDE); MAGNESIUM CARBONATE HYDROXIDE; CITRIC ACID MONOHYDRATE; METHYLCHLOROISOTHIAZOLINONE; METHYLISOTHIAZOLINONE; WATER; FD&C BLUE NO. 1; D&C RED NO. 33

Studio Selection 311.007/311AK-AN
Everyday Clean 2 in 1 Dandruff Shampoo

Claims

Multiple benefit formula to help:

- Fight dry scalp
- Calm itch
- Relieve irritation
- Soothe and reduce redness
- Reduce oiliness
- Prevent flakes
- Leave hair healthy looking

Active ingredient

Pyrithione Zinc 1%

Purpose

Anti-dandruff

Use

helps prevent recurrence of flaking and itching associated with dandruff

Warnings

For external use only

When using this product

- do not get into eyes. If contact occurs, rinse eyes thoroughly with water.

Stop use and ask a doctor if

- condition worsens or does not improve after regular use as directed

Keep out of reach of children.

If swallowed, get medical help or contact a Poison Control Center right away.

Directions

- shake well
- for maximum dandruff controll, use every time you shampoo
- wet hair, massage onto scalp, rinse, repeat if desired
- for best results use at least twice a week or as directed by a doctor

Inactive ingredients

water, sodium lauryl sulfate, sodium laureth sulfate, glycol distearate, sodium chloride, zinc carbonate, sodium xylenesulfonate, amodimethicone, cocamidopropyl betaine, fragrance, sodium benzoate, guar hydroxypropyltrimonium chloride, magnesium carbonate hydroxide, citric acid, methylchloroisothiazolinone, methylisothiazolinone, blue 1, red 33

Disclaimer

*This product is not manufactured or distributed by Procter & Gamble, the distributor of Head & Shoulders® 2in1 Classic Clean Dandruff Shampoo + Conditioner.

Adverse Reactions

DISTRIBUTED BY OLD EAST MAIN CO.

100 MISSION RIDGE

GOODLETTSVILLE, TN 37072

100% Satisfaction Guaranteed!

(888)309-9030

Principal display panel

STUDIO SELECTION®

SIMPLY

CLEAN

DANDRUFF SHAMPOO

+ CONDITIONER

PYRITHIONE ZINC 1%

Compare to Head & Shoulders®Classic Clean 2in1 Dandruff Shampoo + Conditioner*

For normal or oily hair

2 in 1

PARABEN + PHTHALATE FREE

12.5 FL OZ (370 mL)